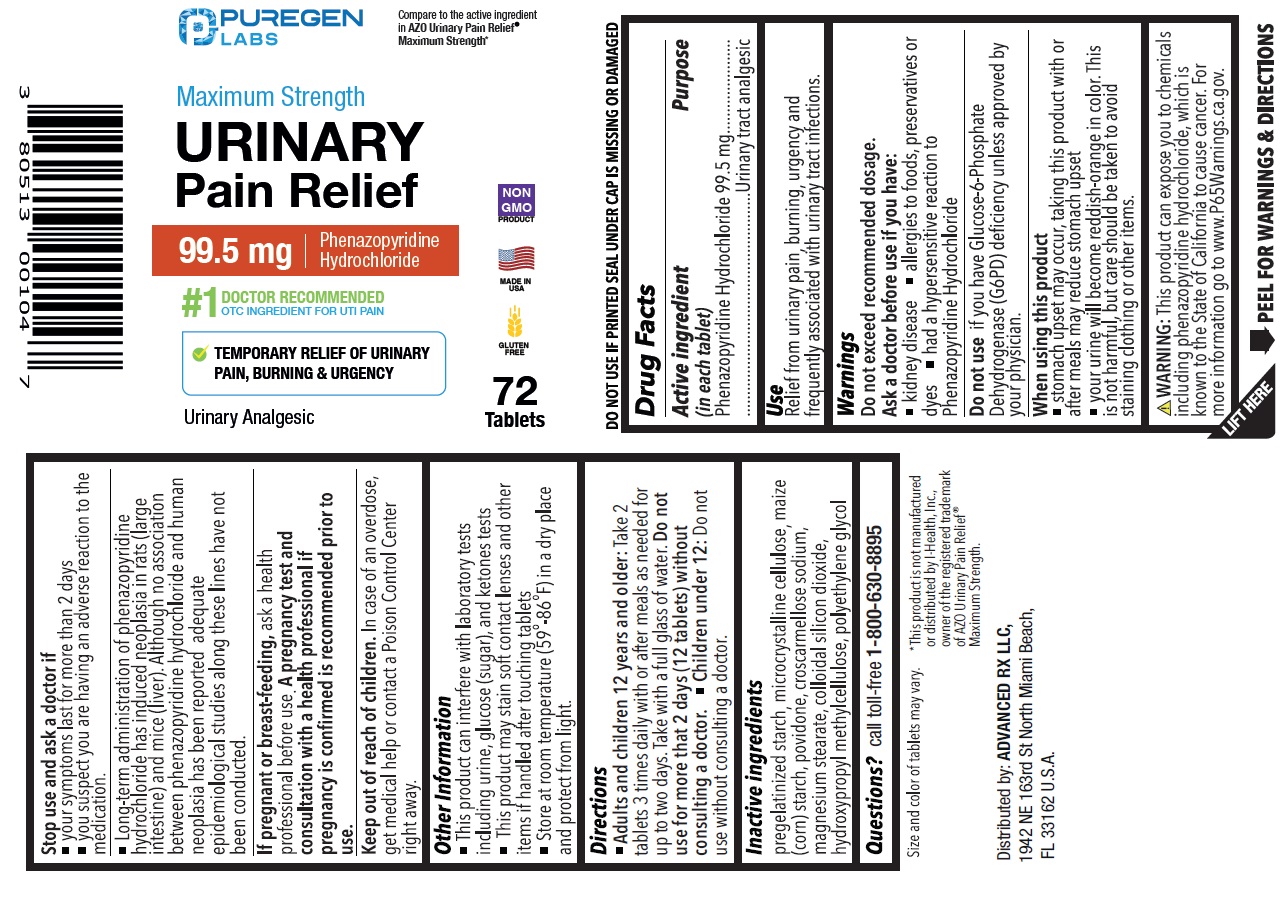 DRUG LABEL: Maximum Strength Urinary Pain Relief
NDC: 80513-517 | Form: TABLET
Manufacturer: Advanced Rx LLC
Category: otc | Type: HUMAN OTC DRUG LABEL
Date: 20240501

ACTIVE INGREDIENTS: PHENAZOPYRIDINE HYDROCHLORIDE 99.5 mg/1 1
INACTIVE INGREDIENTS: STARCH, CORN; MICROCRYSTALLINE CELLULOSE; POVIDONE; CROSCARMELLOSE SODIUM; MAGNESIUM STEARATE; SILICON DIOXIDE; HYPROMELLOSE, UNSPECIFIED; POLYETHYLENE GLYCOL, UNSPECIFIED

Maximum Strength Urinary Pain Relief

Active ingredient (in each tablet)

Phenazopyridine Hydrochloride 99.5 mg

Purpose

Urinary tract analgesic

Use

Relief from urinary pain, burning, urgency and frequency associated with urinary tract infections.

Warnings

Do not exceed recommended dosage.

Ask a doctor before use if you have:

• kidney disease

• allergies to foods, preservatives or dyes

• had a hypersensitive reaction to Phenazopyridine Hydrochloride

Do not useif you have Glucose-6-Phosphate Dehydrogenase (G6PD) deficiency unless approved by your physician.

When using this product

• stomach upset may occur, taking this product with or after meals may reduce stomach upset

• your urine will become reddish-orange in color. This is not harmful, but care should be taken to avoid staining clothing or other items.

Stop use and ask a doctor if

• your symptoms last for more than 2 days

• you suspect you are having an adverse reaction to the medication.

• Long-term administration of phenazopyridine hydrochloride has induced neoplasia in rats (large intestine) and mice (liver). Although no association between phenazopyridine hydrochloride and human neoplasia has been reported, adequate epidemiological studies along these lines have not been conducted.

If pregnant or breastfeeding, ask a health professional before use. A pregnancy test and consultation with a health professional if pregnancy is confirmed is recommended prior to use.

Keep out of reach of children.In case of an overdose, get medical help or contact a Poison Control Center right away.

Other information

• This product can interfere with laboratory tests including urine, glucose (sugar), and ketones tests

• This product may stain contact lenses and other items if handled after touching tablets.

• Store at room temperature between (59ºF -86ºF) in a dry place and protect from light.

Directions

• Adults and children 12 years and older:Take 2 tablets 3 times daily with or after meals as needed for up to two days. Take with a full glass of water. Do not use for more than 2 days (12 tablets) without consulting a doctor.

• Children under 12 years:Do not use without consulting a doctor

Inactive ingredients

pregelatinized starch, microcrystalline cellulose, maize (corn) strach, povidone, croscarmellose sodium, magnesium stearate, colloidal silicone dioxide, hydroxypropyl methylcellulose, polyethylene glycol.

Questions?

call toll-free 1-800-630-8895

PACKAGE LABEL

Compare to the active ingredient in AZO Urinary Pain Relief®Maximum Strength*

NDC 80513-517-72

Maximum Strength Urinary Pain Relief

99.5 mg Phenazopyridine Hydrochloride

#1 DOCTOR RECOMMENDED OTC INGREDIENT FOR UTI PAIN

TEMPORARY RELIEF OF URINARY PAIN, BURNING & URGENCY

Urinary Analgesic

72 Tablets

DO NOT USE IF PRINTED SEAL UNDER CAP IS MISSING OR DAMAGED

Size and color of tablet may very.

WARNING: This product can expose you to chemicals including phenazopyridine hydrochloride, which is known to the State of California to cause cancer. For more information go to www.P65Warnings.ca.gov.

*This product is not manufactured or distributed by I-Health, Inc., owner of the registered trademark of AZO Urinary Pain Relief®Maximum Strength

Distributed by:

ADVANCED RX LLC,

1942 NE 163rd St North Miami Beach,

FL 33162 U.S.A.

MADE IN USA